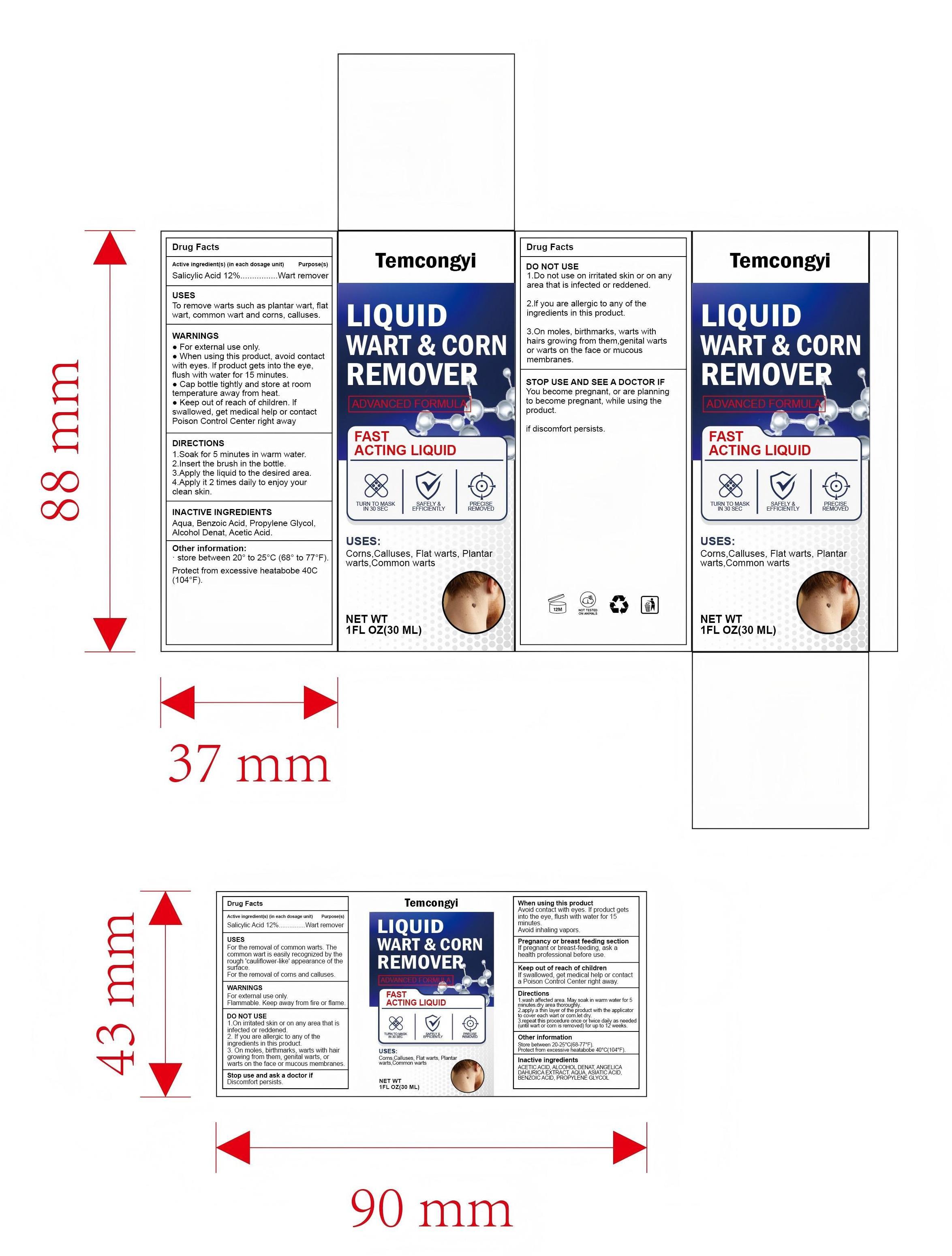 DRUG LABEL: Temcongyi
NDC: 87066-5827 | Form: LIQUID
Manufacturer: Hubei Redrui Building Materials Co., Ltd.
Category: otc | Type: HUMAN OTC DRUG LABEL
Date: 20250826

ACTIVE INGREDIENTS: SALICYLIC ACID 3.6 g/30 g
INACTIVE INGREDIENTS: AQUA 21.285 g/30 g; ACETIC ACID 1 g/30 g; BENZOIC ACID 0.015 g/30 g; PROPYLENE GLYCOL 1.5 g/30 g; ASIATIC ACID 1 g/30 g; ALCOHOL 0.6 g/30 g; ANGELICA DAHURICA ROOT 1 g/30 g

Active ingredient(s)

Salicylic acid 12%

Purpose(s)

Wart and corn remover

Uses

- For the removal of common warts. The common wart is easily recognized by the rough 'cauliflower-like' appearance of the surface.
- For the removal of corns and calluses.

Warnings

- For external use only.
- Flammable. Keep away from fire or flame.

Do not use

- On irritated skin or on any area that is infected or reddened.
- If you are allergic to any of the ingredients in this product.
- On moles, birthmarks, warts with hair growing from them, genital warts, or warts on the face or mucous membranes.

When using this product

- Avoid contact with eyes. If product gets into the eye, flush with water for 15 minutes.
- Avoid inhaling vapors.
- Cap bottle tightly when not in use.

Stop use and ask a doctor if

- Discomfort persists.

Pregnancy or breast feeding section

If pregnant or breast-feeding, ask a health professional before use.

Keep out of reach of children

If swallowed, get medical help or contact a Poison Control Center right away.

Directions

- Wash affected area.
- May soak wart in warm water for 5 minutes.
- Dry area thoroughly.
- Using the applicator, apply the liquid one drop at a time to sufficiently cover each wart, corn, or callus.
- Let dry.
- Repeat this procedure once or twice daily as needed (until wart, corn or callus is removed) for up to 12 weeks.

Other information

- Store between 20-25℃(68-77℉). Protect from excessive heatabobe 40℃(104℉).

Inactive ingredients

ACETIC ACID, ALCOHOL, ANGELICA DAHURICA ROOT, AQUA, ASIATIC ACID, BENZOIC ACID, PROPYLENE GLYCOL

Questions or comments?

934-935-7135 / Yiqinzhi726@gmail.com

Box Front Panel

ADVANCED FORMULA
FAST ACTING LIQUID
TURN TO MASK IN 30 SEC
SAFELY & EFFICIENTLY
PRECISE REMOVED